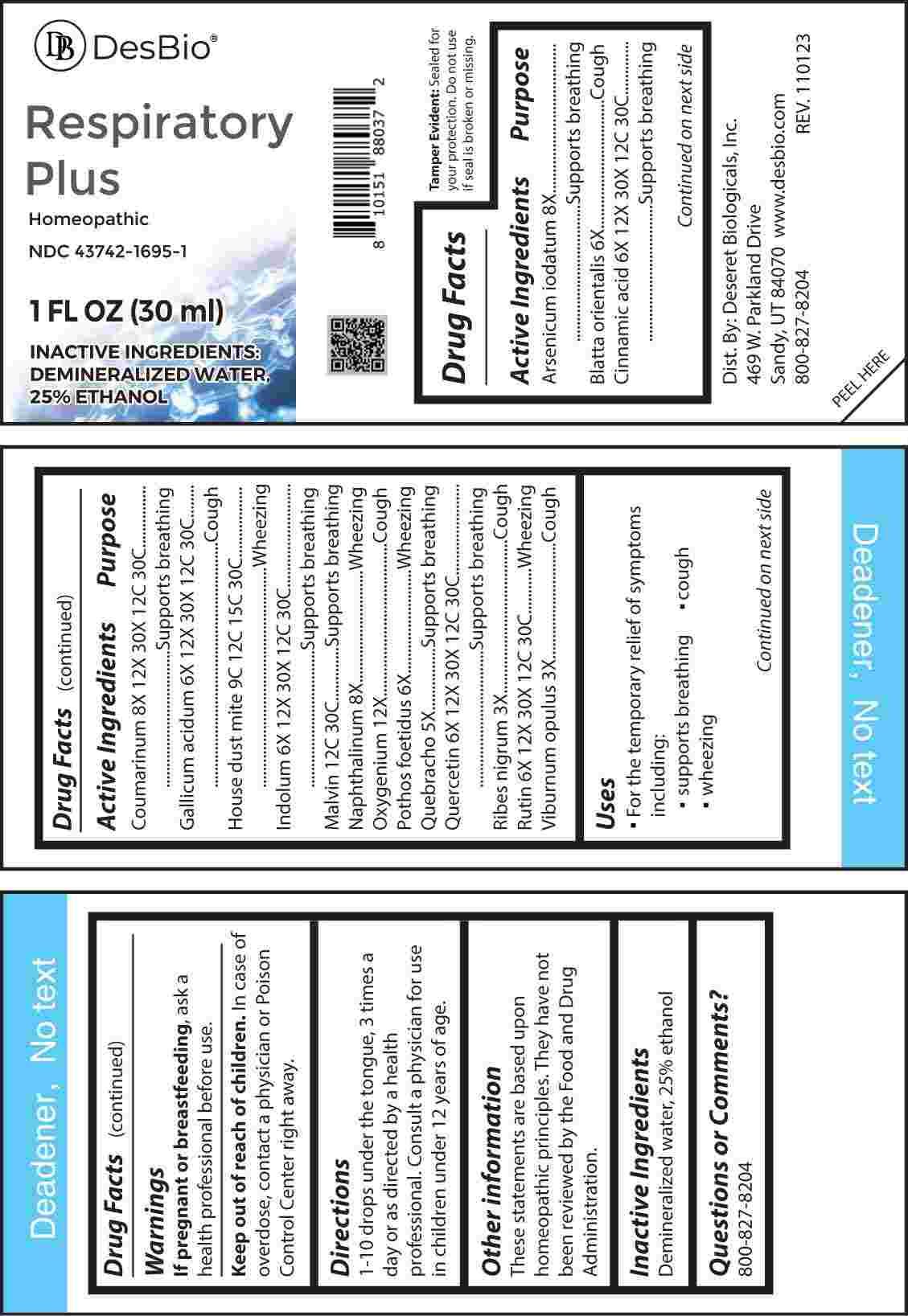 DRUG LABEL: Respiratory Plus
NDC: 43742-1695 | Form: LIQUID
Manufacturer: Deseret Biologicals, Inc.
Category: homeopathic | Type: HUMAN PRESCRIPTION DRUG LABEL
Date: 20240820

ACTIVE INGREDIENTS: RIBES NIGRUM LEAF 3 [hp_X]/1 mL; VIBURNUM OPULUS BARK 3 [hp_X]/1 mL; ASPIDOSPERMA QUEBRACHO-BLANCO BARK 5 [hp_X]/1 mL; BLATTA ORIENTALIS 6 [hp_X]/1 mL; SYMPLOCARPUS FOETIDUS ROOT 6 [hp_X]/1 mL; CINNAMIC ACID 6 [hp_X]/1 mL; GALLIC ACID MONOHYDRATE 6 [hp_X]/1 mL; INDOLE 6 [hp_X]/1 mL; QUERCETIN 6 [hp_X]/1 mL; RUTIN 6 [hp_X]/1 mL; ARSENIC TRIIODIDE 8 [hp_X]/1 mL; NAPHTHALENE 8 [hp_X]/1 mL; COUMARIN 8 [hp_X]/1 mL; OXYGEN 12 [hp_X]/1 mL; DERMATOPHAGOIDES FARINAE 9 [hp_C]/1 mL; MALVIN 12 [hp_C]/1 mL
INACTIVE INGREDIENTS: WATER; ALCOHOL

DRUG FACTS:

ACTIVE INGREDIENTS:

Arsenicum Iodatum 8X, Blatta Orientalis 6X, Cinnamic Acid 6X, 12X, 30X, 12C, 30C, Coumarinum 8X, 12X, 30X, 12C, 30C, Gallicum Acidum 6X, 12X, 30X, 12C, 30C, House Dust Mite 9C, 12C, 15C, 30C, Indolum 6X, 12X, 30X, 12C, 30C, Malvin 12C, 30C, Naphthalinum 8X, Oxygenium 12X, Pothos Foetidus 6X, Quebracho 5X, Quercetin 6X, 12X, 30X, 12C, 30C, Ribes Nigrum 3X, Rutin 6X, 12X, 30X, 12C, 30C, Viburnum Opulus 3X.

PURPOSE:

Arsenicum Iodatum – Supports breathing, Blatta Orientalis - Cough, Cinnamic Acid – Supports breathing, Coumarinum - Supports breathing, Gallicum Acidum - Cough, House Dust Mite - Wheezing, Indolum - Supports breathing, Malvin - Supports breathing, Naphthalinum - Wheezing, Oxygenium - Cough, Pothos Foetidus - Wheezing, Quebracho - Supports breathing, Quercetin - Supports breathing, Ribes Nigrum - Cough, Rutin - Wheezing, Viburnum Opulus - Cough

USES:

• For the temporary relief of symptoms including:

• supports breathing • cough • wheezing

These statements are based upon homeopathic principles. They have not been reviewed by the Food and Drug Administration.

WARNINGS:

If pregnant or breast-feeding, ask a health professional before use.

Keep out of reach of children. In case of overdose, contact a physician or Poison Control Center right away.

Tamper Evident: Sealed for your protection. Do not use if seal is broken or missing.

KEEP OUT OF REACH OF CHILDREN:

In case of overdose, contact a physician or Poison Control Center right away.

DIRECTIONS:

1-10 drops under the tongue, 3 times a day or as directed by a health professional. Consult a physician for use in children under 12 years of age.

INACTIVE INGREDIENTS:

Demineralized water, 25% ethanol

QUESTIONS:

Dist. By: Deseret Biologicals, Inc.
469 W. Parkland Drive
Sandy, UT 84070

www.desbio.com

800-827-8204

PACKAGE LABEL DISPLAY:

Des Bio

Respiratory

Plus

Homeopathic

NDC 43742-1695-1

1 FL OZ (30 ml)